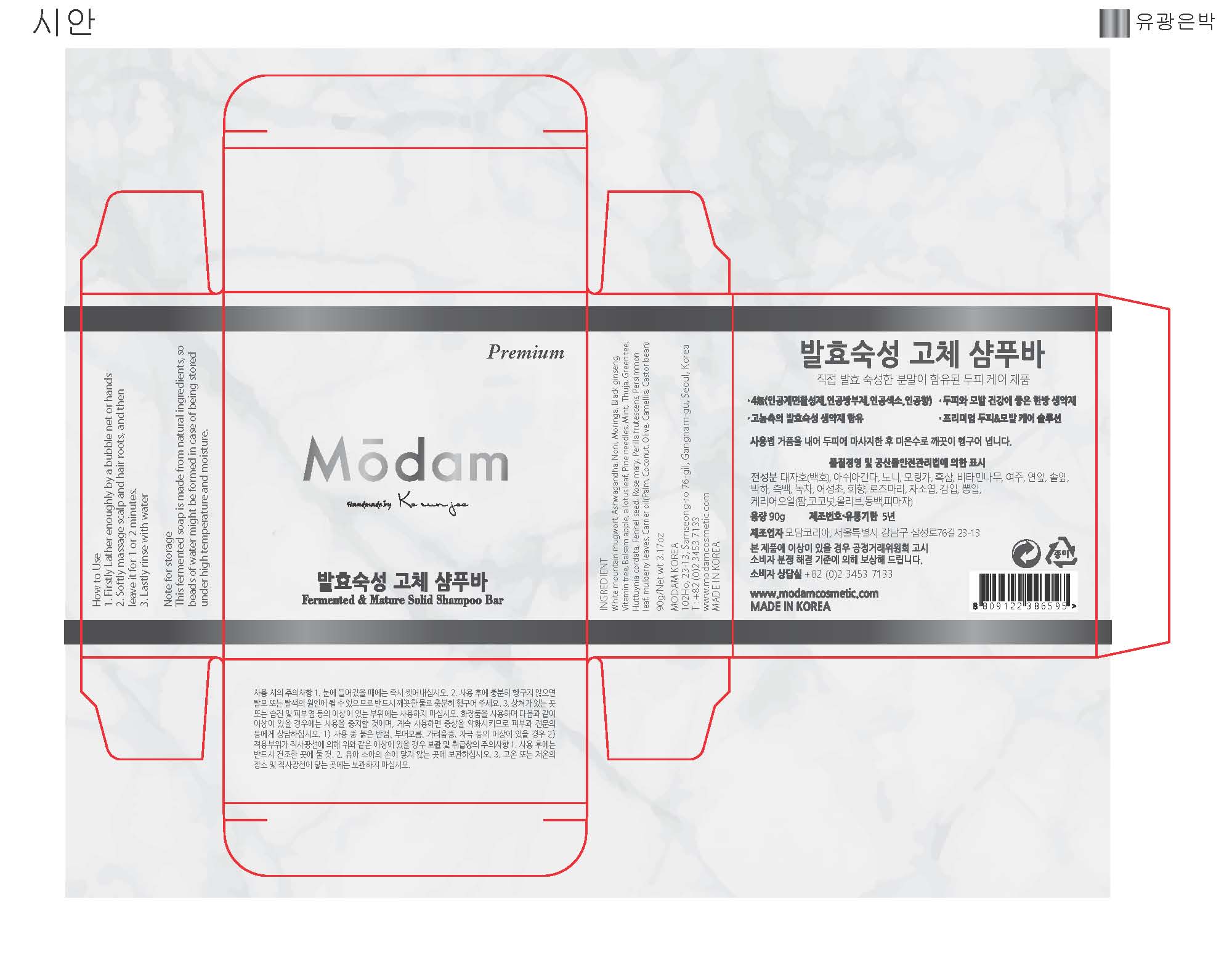 DRUG LABEL: Natural Fermented and Ripen Modam
NDC: 72540-001 | Form: LIQUID
Manufacturer: MODAM KOREA
Category: otc | Type: HUMAN OTC DRUG LABEL
Date: 20190508

ACTIVE INGREDIENTS: OLEA EUROPAEA FRUIT VOLATILE OIL 20.7 g/90 g
INACTIVE INGREDIENTS: CAMELLIA JAPONICA SEED OIL; PINUS DENSIFLORA LEAF; DIOSPYROS KAKI LEAF

ACTIVE INGREDIENT

N/A

INACTIVE INGREDIENT

White mountain mugwort, Ashwagandha, Noni, Moringa, Black ginseng,
Vitamin tree, Balsam apple, a lotus leaf, Pine needles, Mint, Thuja, Green tee,
Huttuynia cordata, Fennel seed, Rose mary, Perilla frutescens, Persimmon
leaf, mulberry leaves, Carrier oil(Palm, Coconut, Olive, Camellia, Castor bean)

PURPOSE

Hair & Scalp Care

WARNINGS

Precautions of Use

- In case of contact with eyes, wash immediately

- If you do not rinse thoroughly after use, it may cause hair loss or discoloration, so please rinse thoroughly with clean water.

- Please do not use the area where there is a wound or eczema and dermatitis.

- Stop using and see a doctor 1) If you have abnormalities such as red spots, swelling, itching, irritation during use 2) If there is any abnormality such as above due to direct sunlight

INDICATIONS & USAGE

How to Use
1. Firstly Lather enoughly by a bubble net or hands
2. Softly massage scalp and hair roots, and then
leave it for 1 or 2 minutes.
3. Lastly rinse with water

Note for storage
This fermented soap is made from natural ingredients, so
beads of water might be formed in case of being stored
under high temperature and moisture.

DOSAGE & ADMINISTRATION

How to Use
1. Firstly Lather enoughly by a bubble net or hands
2. Softly massage scalp and hair roots, and then
leave it for 1 or 2 minutes.
3. Lastly rinse with water

Note for storage
This fermented soap is made from natural ingredients, so
beads of water might be formed in case of being stored
under high temperature and moisture.